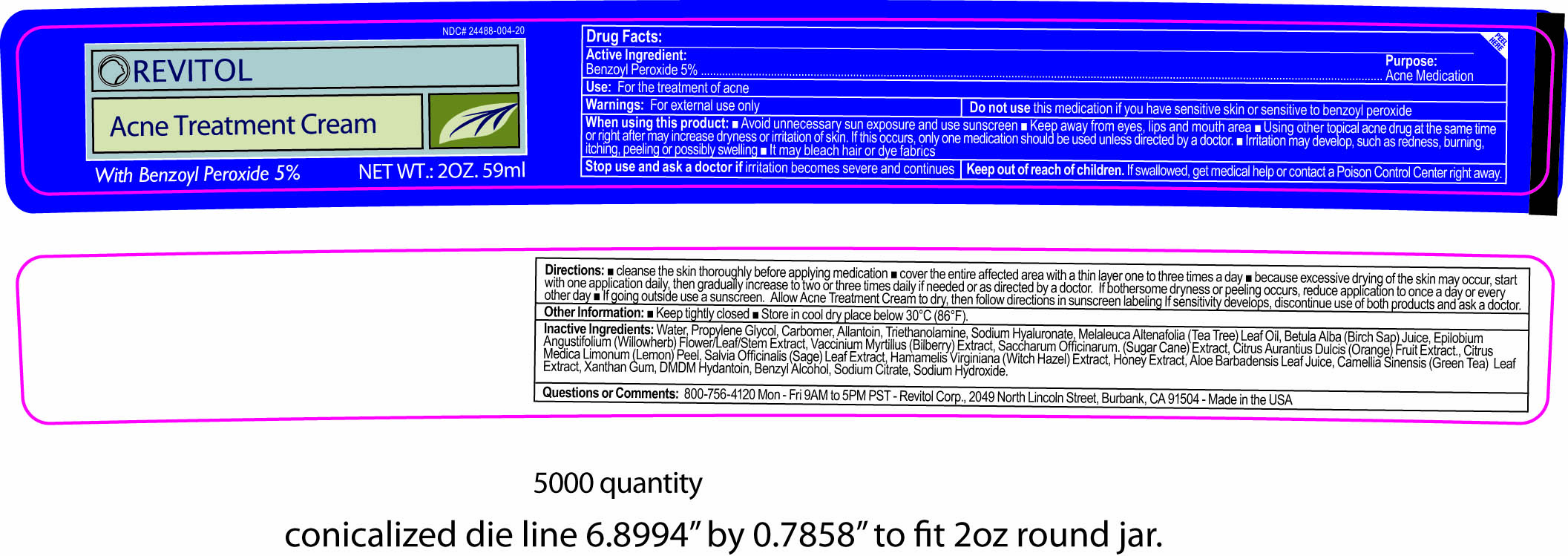 DRUG LABEL: Revitol
NDC: 24488-004 | Form: CREAM
Manufacturer: Revitol Corporation
Category: otc | Type: HUMAN OTC DRUG LABEL
Date: 20110414

ACTIVE INGREDIENTS: BENZOYL PEROXIDE 2.95 mL/59 mL
INACTIVE INGREDIENTS: WATER; PROPYLENE GLYCOL; CARBOMER HOMOPOLYMER TYPE C; ALLANTOIN; TROLAMINE; HYALURONATE SODIUM; TEA TREE OIL; BETULA PUBESCENS RESIN; EPILOBIUM ANGUSTIFOLIUM LEAF; BILBERRY; SUGARCANE; ORANGE; LEMON PEEL; SAGE; HAMAMELIS VIRGINIANA ROOT BARK/STEM BARK; HONEY; ALOE VERA LEAF; GREEN TEA LEAF; XANTHAN GUM; DMDM HYDANTOIN; BENZYL ALCOHOL; SODIUM CITRATE; SODIUM HYDROXIDE

Drug Facts:

Active Ingredient..............................Purpose:

Benzoyl Peroxide 5%..............................Acne Medication

Use:

For the treatment of acne.

Warnings:

For external use only.

Do not use

if you have sensitive skin or are sensitive to benzoyl peroxide.

When using this product:

- Avoid unnecessary sun exposure and use sunscreen.
- Keep away from eyes, lips and mouth areas.
- Using other topical acne drug at the same time or right after may increase dryness or irritation of skin. If this occurs, only one medication should be used unless directed by a doctor.
- Irritation may develop, such as redness, burning, itching, peeling or possibly swelling.
- It may bleach hair or dye fabrics.

Stop use and ask a doctor if

irritation becomes severe and continues

Keep out of reach of children.

if swallowed, get medical help or contact a Poison Control Center right away.

Directions:

- Cleanse the skin thoroughly before applying medication
- Cover the entire affected area with a thin layer one to three times a day
- Because excessive drying of the skin may occur, start with one application daily, then gradually increase to two ore three times daily if needed or as directed by a doctor. If bothersome drying or peeling occurs, reduce application to once a day or every other day.
- If going outside, use a sunscreen. Allow Acne Treatment Cream to dry, then follow directions in sunscreen labeling if sensitivity develops, discontinue use of both products and ask a doctor.

Other Information:

Enter section text here

Inactive Ingredients

Water, Propylene Glycol, Carbomer Allantoin, Triethanolamine, Sodium Hyaluronate, Melaleuca Alternafolia (Tea Tree) Leaf Oil, Betula Alba (Birch Sap) Juice, Epilobium Angustifolium (Willowherb) Flower/Leaf/Stem Extract, Vaccinium Myrtillus (Bilberry) Extract, Saccharum Officinarum (Sugar Cane) Extract, Citrus Aurantius Dulcis (Orange) Fruit Extract, Citrus Medica Limonum (Lemon) Peel, Salvia Officinalis (Sage) Leaf Extract, Hamamelis Virginiana (Witch Hazel) Extract, Honey Extract, Aloe Barbadensis Leaf Juice, Camellia Sinensis (Green Tea) Leaf Extract, Xathan Gum, DMDM Hydantoin, Benzyl Alcohol, Sodium Citrate, Sodium Hydroxide

Questions or Comments:

1-800-756-4120 Mon - Fri 9AM to 5PM PST - Revitol Corp., 2049 North Lincoln Street, Burbank, CA 91504 - Made in the USA

PACKAGE LABEL

Placeholder Text